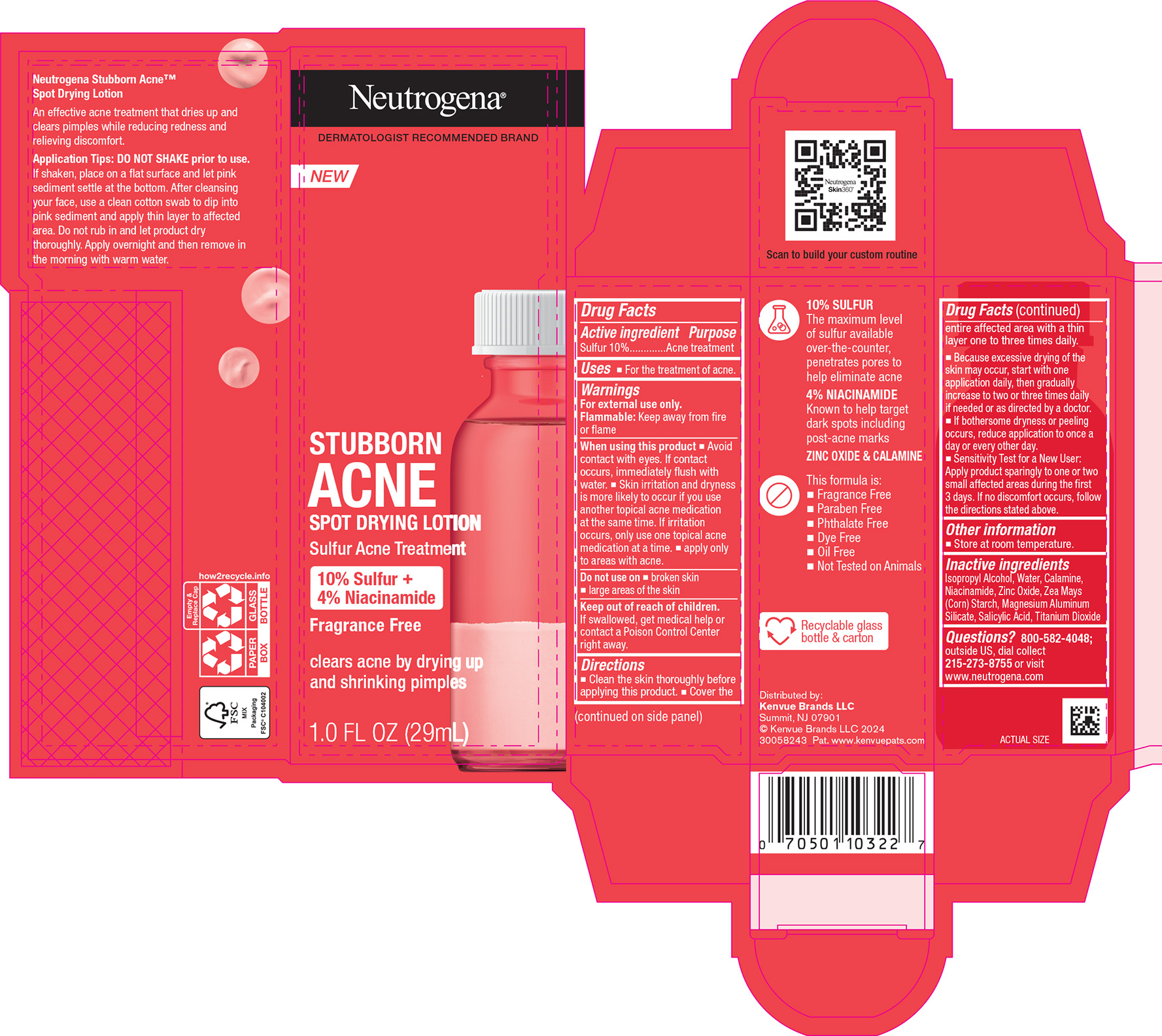 DRUG LABEL: Neutrogena Stubborn Acne Spot Drying
NDC: 69968-0761 | Form: LOTION
Manufacturer: Kenvue Brands LLC
Category: otc | Type: HUMAN OTC DRUG LABEL
Date: 20241126

ACTIVE INGREDIENTS: SULFUR 100 mg/1 mL
INACTIVE INGREDIENTS: ZINC OXIDE; STARCH, CORN; TITANIUM DIOXIDE; WATER; ISOPROPYL ALCOHOL; NIACINAMIDE; MAGNESIUM ALUMINUM SILICATE; SALICYLIC ACID

Neutrogena Stubborn Body Acne Cleanser and Exfoliator

Drug Facts

Active ingredient

Sulfur 10%

Purpose

Acne treatment

Use

For the treatment of acne.

Warnings

For external use only.

Flammable: Keep away from fire or flame

When using this product

- Avoid contact with eyes. If contact occurs, immediately flush with water.
- Skin irritation and dryness is more likely to occur if you use another topical acne medication at the same time. If irritation occurs, only use one topical acne medication at a time.
- apply only to areas with acne.

Do not use on

▪ broken skin ▪ large areas of the skin

Keep out of reach of children. If swallowed, get medical help or contact a Poison Control Center right away.

Directions

- Clean the skin thoroughly before applying this product.
- Cover the entire affected area with a thin layer one to three times daily.
- Because excessive drying of the skin may occur, start with one application daily, then gradually increase to two or three times daily if needed or as directed by a doctor.
- If bothersome dryness or peeling occurs, reduce application to once a day or every other day.
- Sensitivity Test for a New user: Apply product sparingly to one or two small affected areas during the first 3 days. If no discomfort occurs, follow the directions stated above.

Other Information

- Store at room temperature

Inactive ingredients

Isopropyl Alcohol, Water, Calamine, Niacinamide, Zinc Oxide, Zea Mays (Corn) Starch, Magnesium Aluminum Silicate, Salicylic Acid, Titanium Dioxide

Questions?

800-582-4048; outside US, dial collect 215-273-8755 or visit www.neutrogena.com

Distributed by:
Kenvue Brands LLC
Summit, NJ 07901

PRINCIPAL DISPLAY PANEL - 29mL Bottle

Neutrogena®

DERMATOLOGIST RECOMMENDED BRAND

NEW

STUBBORN

ACNE

SPOT DRYING LOTION

Sulfur Acne Treatment

10% Sulfur +

4% Niacinamide

Fragrance Free

clears acne by drying up

and shrinking pimples

1 FL OZ (29mL)